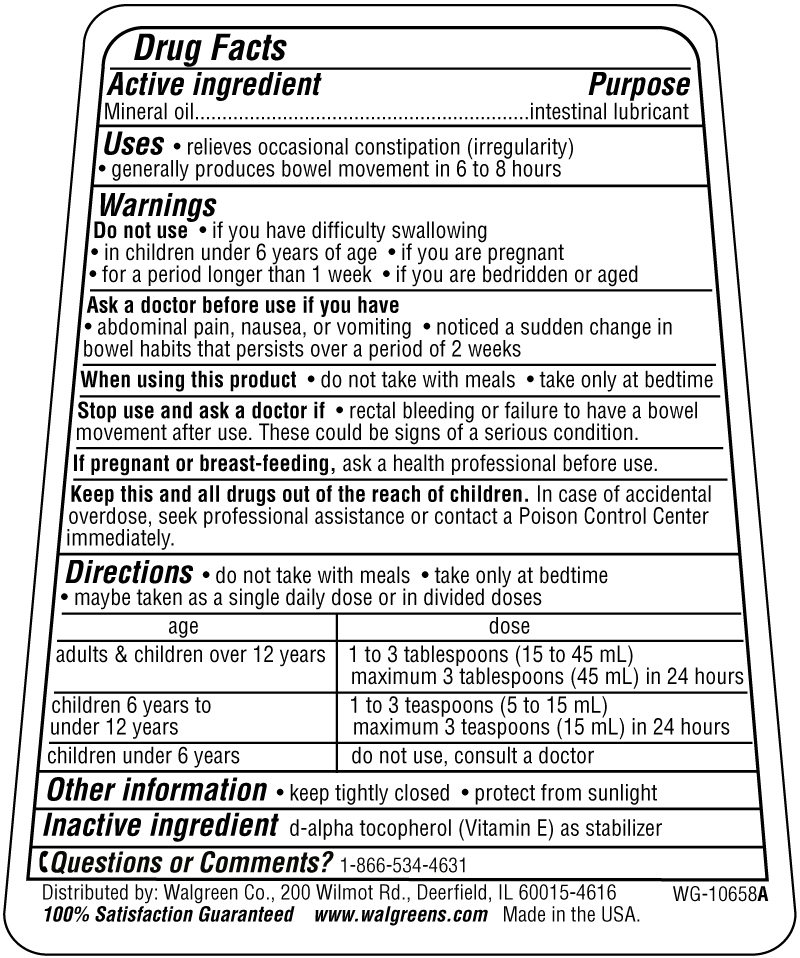 DRUG LABEL: Mineral Oil
NDC: 0363-0360 | Form: OIL
Manufacturer: Walgreens
Category: otc | Type: HUMAN OTC DRUG LABEL
Date: 20091118

ACTIVE INGREDIENTS: MINERAL OIL 15 mL/15 mL
INACTIVE INGREDIENTS: ALPHA-TOCOPHEROL

Drug Facts

Active Ingredient

Mineral Oil

PURPOSE

intestinal lubricant

Uses

relieves occasional constipation (irregularity)

generally produces bowel movement in 6 to 8 hours

Warnings

Do not use

if you have difficulty swallowing

in children under 6 years of age

if you are pregnant

for a period longer than one week

if you are bedridden or aged

Ask a doctor before use if you have

abdominal pain, nausea or vomiting

noticed a sudden change in bowel habits that persists over a period of 2 weeks

When using this product

do not take with meals

take only at bedtime

Stop use and ask a doctor if you have

rectal bleeding or failure to have a bowel movement after use

these could be signs of a serious condition

If pregnant or breast feeding,

ask a health professional before use

Keep this and all drugs out of the reach of children

In case of accidental overdose, seek professional assistance or contact a Poison Control Center immediately

Directions

do not take with meals

take only at bedtime

may be taken as a single daily dose or in divided doses

age dose

adults and children over 12 years 1 to 3 tablespoons (15 to 45 ml)

maximum3 tablespoons (45mL) in 24 hours

children 6 years to under 12 years 1 to 3 tablespoons (15 to 45 ml)

maximum3 tablespoons (45mL) in 24 hours

children under 6 years do not use, consult a doctor

Other Information

keep tightly closed

protect from sunlight

Inactive Ingredient

d-alpha tocopherol (Vitamin E) as stabilizer

Principal Display Panel

Walgreens
Mineral Oil